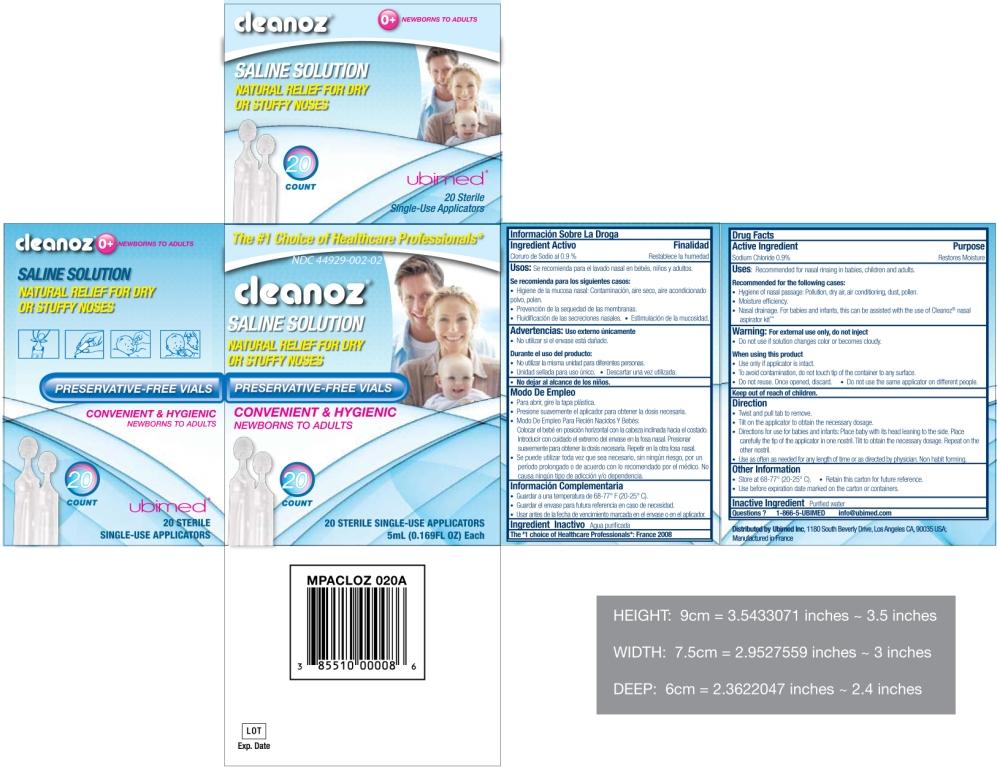 DRUG LABEL: Cleanoz
								
NDC: 44929-002 | Form: SOLUTION
Manufacturer: Laboratoires Gifrer Barbezat
Category: otc | Type: HUMAN OTC DRUG LABEL
Date: 20100311

ACTIVE INGREDIENTS: sodium chloride 900 mg/100 mL
INACTIVE INGREDIENTS: water

Uses

- Recommended for nasal rinsing in babies, children and adults.

Recommended for the following cases:

- Hygiene of nasal passage: Pollution, dry air, airconditioning, dust, pollen.
- Moisture efficiency.
- Nasal drainage. For babies and infants, this can be assisted with the use of Cleanoz® nasal aspirator kitTM

Warning

For external use only, do not inject

- Do not use if solution changes color or becomes cloudy.

When using this product

- Use only if applicator is intact.
- To avoid contamination, do not touch tip of the container to any surface.
- Do not reuse. Once opened, discard.
- Do not use the same applicator on different people.

Direction

- Twist and pull tab to remove.
- Tilt on the applicator to obtain the necessary dosage.
- Directions for use for babies and infants: Place the baby with its head leaning to the side. Place carefully the tip of the applicator in one nostril. Tilt to obtain the necessary dosage. Repeat on the other nostril.
- Use as often as needed for any length of time or as directed by physician. Non habit forming.

Other information

- Store at 68-77°F (20-25°C).
- Retain this carton for future reference.
- Use before expiration date marked on the carton or containers.

Inactive ingredients

Purified water, 0.9% Sodium Chloride

Questions? 1-866-5-UBIMED info@ubimed.com

Principal Display Panel

Cleanoz(R)

Saline solution

Natural relief for dry or stuffy noses

Convenient and hygienic

Newborns to adults

The #1 Choice of Healthcare Professionals

Preservative-free vials

Ubimed

3/5/10/20/30/40 Count

3/5/10/20/30/40 Sterile Single-Use Applicators

5mL (0.169 FL OZ) Each